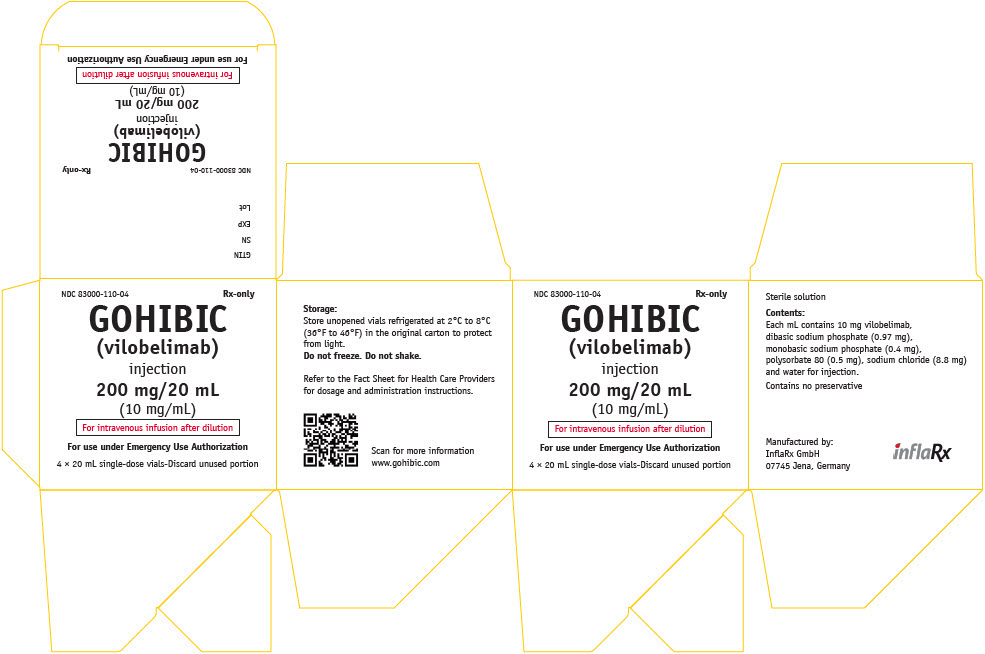 DRUG LABEL: GOHIBIC
NDC: 83000-110 | Form: INJECTION
Manufacturer: InflaRx GmbH
Category: prescription | Type: HUMAN PRESCRIPTION DRUG LABEL
Date: 20250123

ACTIVE INGREDIENTS: VILOBELIMAB 10 mg/1 mL
INACTIVE INGREDIENTS: SODIUM CHLORIDE; SODIUM PHOSPHATE, MONOBASIC, DIHYDRATE; SODIUM PHOSPHATE, DIBASIC, DIHYDRATE; POLYSORBATE 80

FACT SHEET FOR HEALTHCARE PROVIDERS: EMERGENCY USE AUTHORIZATION FOR GOHIBIC
HIGHLIGHTS OF EMERGENCY USE AUTHORIZATION (EUA) These highlights of the EUA do not include all the information needed to use GOHIBIC under the EUA. See FULL FACT SHEET FOR HEALTHCARE PROVDERSfor GOHIBIC. |  | ---------------------DOSAGE FORMS AND STRENGTHS--------------------- Injection: 200 mg/20 mL (10 mg/mL) in single-dose vials for further dilution. (3)
GOHIBIC (vilobelimab) injection, for intravenous use Original EUA Authorized Date: 04/2023 Revised EUA Authorized Date: 05/2023 |  | -------------------------------CONTRAINDICATIONS----------------------------- No contraindications have been identified based on limited available data on emergency use of GOHIBIC authorized under this EUA. (4)
------------------------RECENT MAJOR CHANGES-----------------------
Emergency Use Authorization (1): revision to Information Regarding
Available Alternatives for the EUA Authorized Use 05/2023
--------EMERGENCY USE AUTHORIZATION FOR GOHIBIC------- The U.S. Food and Drug Administration has issued an EUA for the emergency use of GOHIBIC for the treatment of coronavirus disease 19 (COVID-19) in hospitalized adults when initiated within 48 hours of receiving invasive mechanical ventilation (IMV), or extracorporeal membrane oxygenation (ECMO). However, GOHIBIC is not FDA-approved for this use. (1) See Full Fact Sheet for Healthcare Providersfor the justification for emergency use of drugs during the COVID-19 pandemic, information on available alternatives, and additional information on COVID-19. |  | ------------------------WARNINGS AND PRECAUTIONS-----------------------; - GOHIBIC has been associated with an increase of serious infections. (5.1) - Hypersensitivity reactions have been reported. (5.2)
--------EMERGENCY USE AUTHORIZATION FOR GOHIBIC------- The U.S. Food and Drug Administration has issued an EUA for the emergency use of GOHIBIC for the treatment of coronavirus disease 19 (COVID-19) in hospitalized adults when initiated within 48 hours of receiving invasive mechanical ventilation (IMV), or extracorporeal membrane oxygenation (ECMO). However, GOHIBIC is not FDA-approved for this use. (1) See Full Fact Sheet for Healthcare Providersfor the justification for emergency use of drugs during the COVID-19 pandemic, information on available alternatives, and additional information on COVID-19. |  | -------------------------------ADVERSE REACTIONS------------------------------ The most common adverse reactions (incidence ≥3%) are pneumonia, sepsis, delirium, pulmonary embolism, hypertension, pneumothorax, deep vein thrombosis, herpes simplex, enterococcal infection, bronchopulmonary aspergillosis, hepatic enzyme increased, urinary tract infection, hypoxia, thrombocytopenia, pneumomediastinum, respiratory tract infection, supraventricular tachycardia, constipation, and rash. (6.1)
----------------------DOSAGE AND ADMINISTRATION------------------; - Recommended dosage of GOHIBIC is 800 mg administered by intravenous infusion after dilution, for a maximum of 6 (six) doses over the treatment period as described below. (2.1) - Start treatment within 48 hours of intubation (Day 1), followed by administration of GOHIBIC on Days 2, 4, 8, 15 and 22 as long as the patient is still hospitalized (even if discharged from ICU). (2.1) |  | You or your designee must report all SERIOUS ADVERSE EVENTS or MEDICATION ERRORS potentially related to GOHIBIC by (1) submitting FDA Form 3500 online, (2) by downloading this form and then submitting by mail or fax, or (3) contacting the FDA at 1-800-FDA-1088 to request this form. Please also provide a copy of this form to InflaRx GmbH at pvusa@inflarx.de (6.3)
Preparation and Administration; - Dilute 80 mL of GOHIBIC in 170 mL of 0.9% Sodium Chloride at room temperature using aseptic technique. (2.2) - Administer diluted GOHIBIC via intravenous infusion over 30 – 60 minutes. (2.2) |  | --------------------------USE IN SPECIFIC POPULATIONS---------------------; - Lactation:Discontinue drug or nursing taking into consideration importance of drug to mother. (8.2)
 |  | See PATIENT AND CAREGIVER FACT SHEET.

FULL PRESCRIBING INFORMATION: CONTENTS*

1. EMERGENCY USE AUTHORIZATION
2. DOSAGE AND ADMINISTRATION
  - 2.1 Recommended Dosage
  - 2.2 Preparation and Administration
3. DOSAGE FORMS AND STRENGTHS
4. CONTRAINDICATIONS
5. WARNINGS AND PRECAUTIONS
  1. 5.1 Serious Infections
  2. 5.2 Hypersensitivity Reactions
6. ADVERSE REACTIONS
  1. 6.1 Clinical Trial Experience
  2. 6.3 Required Reporting for Serious Adverse Events and Medication Errors
7. DRUG INTERACTIONS
8. USE IN SPECIFIC POPULATIONS
  1. 8.1 Pregnancy
  2. 8.2 Lactation
  3. 8.3 Pediatric Use
  4. 8.4 Geriatric Use

1. DESCRIPTION
2. CLINICAL PHARMACOLOGY
  1. 12.1 Mechanism of Action
  2. 12.2 Pharmacodynamics
  3. 12.3 Pharmacokinetics
  4. 12.6 Immunogenicity
3. NONCLINICAL TOXICOLOGY
  1. 13.1 Carcinogenesis, Mutagenesis, Impairment of Fertility
4. CLINICAL STUDIES
5. HOW SUPPLIED/STORAGE AND HANDLING
6. PATIENT COUNSELING INFORMATION
7. MANUFACTURER INFORMATION

* Sections or subsections omitted from the EUA are not listed.

FULL FACT SHEET FOR HEALTHCARE PROVIDERS

1 EMERGENCY USE AUTHORIZATION

The U.S. Food and Drug Administration (FDA) has issued an Emergency Use Authorization (EUA) for the emergency use of GOHIBIC for the treatment of coronavirus disease 2019 (COVID-19) in hospitalized adults when initiated within 48 hours of receiving invasive mechanical ventilation (IMV), or extracorporeal membrane oxygenation (ECMO). However, GOHIBIC is not FDA-approved for this use.

Justification for Emergency Use of Drugs During the COVID-19 Pandemic

There is currently an outbreak of Coronavirus Disease 2019 (COVID-19) caused by SARS-CoV-2, a novel coronavirus. The Secretary of HHS has:

- Determined that there is a public health emergency, or significant potential for a public health emergency, related to COVID-19 [See U.S. Department of Health and Human Services, Determination of a Public Health Emergency and Declaration that Circumstances Exist Justifying Authorizations Pursuant to Section 564(b) of the Federal Food, Drug, and Cosmetic Act, 21 U.S.C. § 360bbb-3. February 4, 2020; https://www.federalregister.gov/documents/2020/02/07/2020-02496/determination-of-public-health-emergency. See also U.S. Department of Health and Human Services, Amended Determination of a Public Health Emergency or Significant Potential for a Public Health Emergency Pursuant to Section 564(b) of the Federal Food, Drug, and Cosmetic Act, 21 U.S.C. § 360bbb-3(b). March 15, 2023 ("Amended Determination"); https://www.federalregister.gov/documents/2023/03/20/2023-05609/covid-19-emergency-use-authorization-declaration.] .
- Declared that circumstances exist justifying the authorization of emergency use of drugs and biological products for the prevention or treatment of COVID-19 [See U.S. Department of Health and Human Services, Declaration that Circumstances Exist Justifying Authorizations Pursuant to Section 564(b) of the Federal Food, Drug, and Cosmetic Act, 21 U.S.C. § 360bbb-3, 85 FR 18250 (April 1, 2020); https://www.federalregister.gov/documents/2020/04/01/2020-06905/emergency-use-authorization-declaration. See also Amended Determination ("The declarations issued pursuant to section 564(b)(1) of the FD&C Act that circumstances exist justifying the authorization of emergency use of certain in vitro diagnostics, personal respiratory protective devices, other medical devices and drugs and biological products, as set forth in those declarations, and that are based on the February 4, 2020 determination, remain in effect until those declarations are terminated in accordance with section 564 of the FD&C Act.").] .

An EUA is a FDA authorization for the emergency use of an unapproved product or unapproved use of an approved product (i.e., drug, biological product, or device) in the United States under certain circumstances, including, but not limited to, when the Secretary of HHS declares that there is a public health emergency, or significant potential for a public health emergency that affects the national security or the health and security of United States citizens living abroad, and that involves biological agent(s) or a disease or condition that may be attributable to such agent(s). Criteria for issuing an EUA include:

- The biological agent(s) can cause a serious or life-threatening disease or condition;
- Based on the totality of the available scientific evidence (including data from adequate and well-controlled clinical trials, if available), it is reasonable to believe that:
  - The product may be effective in diagnosing, treating, or preventing the serious or life-threatening disease or condition; and
  - The known and potential benefits of the product – when used to diagnose, prevent or treat such disease or condition – outweigh the known and potential risks of the product, taking into consideration the material threat posed by the biological agent(s)
- There is no adequate, approved, and available alternative to the product for diagnosing, preventing, or treating the serious or life-threatening disease or condition.

Information Regarding Available Alternatives for the EUA Authorized Use [This section only describes the uses for which an FDA-approved drug is considered to be an alternative to GOHIBIC. For additional information, including the full indications for the FDA-approved drugs referenced within this section, please refer to the relevant Prescribing Information at: Drugs@FDA: FDA-Approved Drugs. As stated in the Letter of Authorization, the emergency use of GOHIBIC must be consistent with the terms and conditions of its authorization.]

Veklury (remdesivir), a SARS-CoV-2 nucleotide analog RNA polymerase inhibitor, is an FDA-approved alternative to GOHIBIC when used for the treatment of COVID-19 in hospitalized adults and when initiated within 48 hours of receiving IMV, or ECMO. Veklury has demonstrated antiviral activity against SARS-CoV-2; whereas GOHIBIC acts by binding to C5a to block its interaction with the C5a receptor, both of which are components of the complement system thought to contribute to inflammation and worsening of COVID-19, offering a different mechanism of action.

Olumiant (baricitinib), a Janus kinase (JAK) inhibitor, is an FDA-approved alternative to GOHIBIC when used for the treatment of COVID-19 in hospitalized adults and when initiated within 48 hours of requiring IMV, or ECMO. As noted, GOHIBIC offers a different mechanism of action. In addition, GOHIBIC has an intravenous route of administration; whereas, Olumiant is available as tablets, offering an alternative route of administration to adult patients who are mechanically ventilated or on ECMO.

Actemra (tocilizumab), an interleukin-6 (IL-6) receptor antagonist, is an FDA-approved alternative to GOHIBIC when used for the treatment of COVID-19 in hospitalized adults and when initiated within 48 hours of receiving IMV, or ECMO. As noted, GOHIBIC offers a different mechanism of action.

Other therapeutics are currently authorized for the same use as GOHIBIC. For additional information on all products authorized for the treatment of COVID-19, please see https://www.fda.gov/emergency-preparedness-and-response/mcm-legal-regulatory-and-policy-framework/emergency-use-authorization.

For information on clinical studies of GOHIBIC and other therapies for the treatment of COVID-19, see www.clinicaltrials.gov.

2 DOSAGE AND ADMINISTRATION

2.1 Recommended Dosage

The recommended dosage of GOHIBIC for the treatment of adults with COVID-19 is 800 mg administered by intravenous infusion after dilution [see Dosage and Administration (2.2)] for a maximum of 6 (six) doses over the treatment period as described below.

Treatment should be started within 48 hours of intubation (Day 1) followed by administration on Days 2, 4, 8, 15 and 22 as long as the patient is hospitalized (even if discharged from ICU).

2.2 Preparation and Administration

Preparation

Using aseptic technique, dilute and prepare GOHIBIC for intravenous infusion before administration.

- For the recommended dose of 800 mg GOHIBIC, dilute 80 mL of GOHIBIC in 170 mL of 0.9% Sodium Chloride at room temperature.
- Use a 250 mL infusion bag of 0.9% Sodium Chloride solution USP and the follow steps below:
  - Withdraw 80 mL of 0.9% Sodium Chloride solution USP from the infusion bag and discard.
  - Withdraw the 80 mL of GOHIBIC from the vials and add slowly to the 0.9% Sodium Chloride solution USP infusion bag to a final concentration of 3.2 mg/mL.
  - To mix the solution, gently invert the bag to avoid foaming.

Storage of Diluted GOHIBIC

- Diluted GOHIBIC must be used within 4 hours when stored at room temperature 20°C to 25°C (68°F to 77°F).
- Diluted GOHIBIC stored under refrigeration at 2°C to 8°C (36°F to 46°F) must be used within 24 hours.
- After removal of diluted GOHIBIC from the refrigerator stored at 2°C to 8°C (36°F to 46°F), it must be left to acclimatize to room temperature prior to administration.

Administration

- Visually inspect for particulate matter and discoloration prior to administration, whenever solution and container permit. Do not use if discoloration or visible particles are present.
- Administer diluted GOHIBIC via intravenous infusion over 30 - 60 minutes.
- Avoid concomitant administration of GOHIBIC with other drugs in the same intravenous line.

3 DOSAGE FORMS AND STRENGTHS

Injection: 200 mg/20 mL (10 mg/mL) clear to slightly opalescent, colorless solution in a single-dose vial.

4 CONTRAINDICATIONS

No contraindications have been identified based on the limited available data for the emergency use of GOHIBIC under this EUA.

5 WARNINGS AND PRECAUTIONS

There are limited clinical data available for GOHIBIC. Serious and unexpected adverse events (AEs) may occur that have not been previously reported with GOHIBIC use.

5.1 Serious Infections

Serious infections due to bacterial, fungal, and viral pathogens have been reported in patients with COVID-19 receiving GOHIBIC. In patients with COVID-19, monitor for signs and symptoms of new infections during and after treatment with GOHIBIC. There is limited information regarding the use of GOHIBIC in patients with COVID-19 and concomitant active serious infections. The risks and benefits of treatment with GOHIBIC in COVID-19 patients with other concurrent infections should be considered [see Adverse Reactions (6)] .

5.2 Hypersensitivity Reactions

Hypersensitivity reactions have been observed with GOHIBIC. If a severe hypersensitivity reaction occurs, administration of GOHIBIC should be discontinued and appropriate therapy initiated.

6 ADVERSE REACTIONS

6.1 Clinical Trial Experience

The following adverse reactions have been observed in the clinical studies of GOHIBIC that supported the EUA. The adverse reaction rates observed in these clinical studies cannot be directly compared to rates in the clinical studies of other products and may not reflect the rates observed in clinical practice.

The safety of GOHIBIC is based on PANAMO, a Phase 3 randomized, placebo-controlled trial in COVID-19 patients requiring IMV or ECMO [see Clinical Studies (14)] . The analysis of adverse reactions included a total of 364 adult patients who received at least one dose of either GOHIBIC (n=175) or placebo (n=189) plus standard of care. Patients received GOHIBIC 800 mg administered by intravenous infusion on Days 1, 2, 4, 8, 15 and 22 or placebo.

During the study, there were 62 deaths in the GOHIBIC arm and 85 deaths in the placebo arm [see Clinical Studies (14)] . Fatal infections occurred in more placebo patients. Nonfatal serious infections occurred in 58 patients (33.1%) in the GOHIBIC arm and in 55 patients (29.1%) in the placebo arm. The most commonly reported nonfatal serious infections with GOHIBIC were pneumonia (18.9% vs 13.8% in placebo), sepsis (14.9% versus 7.4% in placebo), and septic shock (9.1% versus 7.4% in placebo).

Discontinuation of study treatment due to an adverse reaction occurred in 2.9% of the GOHIBIC group and 1.6% of the placebo group. Adverse reactions leading to discontinuation of GOHIBIC included eczema, bronchopulmonary aspergillosis, rash, hemodynamic instability, thrombocytopenia, and multi-organ failure.

The most common adverse reactions occurring in at least 3% of GOHIBIC-treated patients and at least 1% more frequently than observed in the placebo arm are summarized in Table 1.

Table 1. Adverse Reactions that Occurred in ≥3% of Patients Treated with GOHIBIC and at least 1% More Frequently than Observed in the Placebo Arm through Day 60
Adverse Reactions | GOHIBIC + SoC (N=175) |  | Placebo + SoC (N=189)
 | n | (%) | n | (%)
Pneumonia ["Pneumonia" includes preferred terms containing the term "pneumonia"; does not include "COVID-19 pneumonia"] | 55 | (31.4%) | 44 | (23.3%)
Sepsis ["Sepsis" includes preferred terms containing the term "sepsis".] | 38 | (21.7%) | 30 | (15.9%)
Delirium ["Delirium includes the following preferred terms: Delirium, Intensive care unit delirium] | 22 | (12.6%) | 20 | 10.6%)
Pulmonary embolism | 19 | (10.9%) | 17 | (9.0%)
Hypertension | 16 | (9.1%) | 13 | (6.9%)
Pneumothorax | 14 | (8.0%) | 11 | (5.8%)
Deep vein thrombosis | 11 | (6.3%) | 9 | (4.8%)
Herpes simplex | 11 | (6.3%) | 5 | (2.6%)
Enterococcal infection | 10 | (5.7%) | 8 | (4.2%)
Bronchopulmonary aspergillosis | 10 | (5.7%) | 7 | (3.7%)
Hepatic enzyme increased | 9 | (5.1%) | 7 | (3.7%)
Urinary tract infection | 9 | (5.1%) | 6 | (3.2%)
Hypoxia | 8 | (4.6%) | 6 | (3.2%)
Thrombocytopenia | 8 | (4.6%) | 2 | (1.1%)
Pneumomediastinum | 8 | (4.6%) | 0 | (0.0%)
Respiratory tract infection | 7 | (4.0%) | 5 | (2.6%)
Supraventricular tachycardia | 7 | (4.0%) | 1 | (0.5%)
Constipation | 6 | (3.4%) | 3 | (1.6%)
Rash | 6 | (3.4%) | 0 | (0.0%)
SoC = standard of care.
A patient is only listed once (regardless of event numbers) but one patient can be listed in different categories with one or additional reactions

6.3 Required Reporting for Serious Adverse Events and Medication Errors

The prescribing healthcare provider and/or the provider's designee is/are responsible for mandatory reporting of all serious adverse events (SAEs) [SAEs are defined as: Death;A life-threatening AE;Inpatient hospitalization or prolongation of existing hospitalization;A persistent or significant incapacity or substantial disruption of the ability to conduct normal life functions;A congenital anomaly/birth defect;Other important medical event, which may require a medical or surgical intervention to prevent death, a life-threatening event, hospitalization, disability, or congenital anomaly] and medication errors potentially related to GOHIBIC within 7 calendar days from the healthcare provider's awareness of the event, using FDA Form 3500 (for information on how to access this form, see below). The FDA requires that such reports, using FDA Form 3500, include the following:

- Patient demographics and baseline characteristics (e.g., patient identifier, age or date of birth, gender, weight, ethnicity, and race)
- A statement "GOHIBIC use for COVID-19 under Emergency Use Authorization (EUA)" under the " Describe Event, Problem, or Product Use/Medication Error" heading
- Information about the SAE or medication error (e.g., signs and symptoms, test/laboratory data, complications, timing of drug initiation in relation to the occurrence of the event, duration of the event, treatments required to mitigate the event, evidence of event improvement/disappearance after stopping or reducing the dosage, evidence of event reappearance after reintroduction, clinical outcomes).
- Patient's preexisting medical conditions and use of concomitant products
- Information about the product (e.g., dosage, route of administration, NDC #).

Submit AE and medication error reports, using Form 3500, to FDA MedWatch using one of the following methods:

- Complete and submit the report online: www.fda.gov/medwatch/report.htm
- Complete and submit a postage-paid FDA Form 3500 (https://www.fda.gov/media/76299/download) and return by:
  - Mail to MedWatch, 5600 Fishers Lane, Rockville, MD 20852-9787, or
  - Fax to 1-800-FDA-0178, or
- Call 1-800-FDA-1088 to request a reporting form

In addition, please provide a copy of all FDA MedWatch forms to:
InflaRx GmbH
Fax: 1-866-728-2630
E-mail: pvusa@inflarx.de
Or call InflaRx GmbH at 1-888-254-0602 to report AEs.

The prescribing healthcare provider and/or the provider's designee is/are responsible for mandatory responses to requests from FDA for information about AEs and medication errors following receipt of GOHIBIC.

7 DRUG INTERACTIONS

No drug interaction studies have been conducted with GOHIBIC.

8 USE IN SPECIFIC POPULATIONS

8.1 Pregnancy

Risk Summary

There are no available data on GOHIBIC use in pregnant women to evaluate for a drug-associated risk of major birth defects, miscarriage or other adverse maternal or fetal outcomes. Placental transfer of monoclonal antibodies such as GOHIBIC is greater during the third trimester of pregnancy; therefore, potential effects on a fetus are likely to be greater during the third trimester of pregnancy. In an enhanced pre- and post-natal (ePPND) study conducted in cynomolgus monkeys, placental transport of GOHIBIC was observed but there was no evidence of fetal harm following intravenous administration of GOHIBIC throughout pregnancy at doses 2.5 times the maximum recommended human dose (MRHD) of 800 mg on a mg/kg basis (see Data) .

The estimated background risk of major birth defects and miscarriage for the indicated population is unknown. All pregnancies have a background risk of birth defect, loss, or other adverse outcomes. In the U.S. general population, the estimated background risk for major birth defects and miscarriage in clinical recognized pregnancies is 2% - 4% and 15% - 20%, respectively.

Data

Animal Data

In the ePPND study, pregnant cynomolgus monkeys received GOHIBIC from GD20 to GD22 (dependent on pregnancy determination), at the beginning of organogenesis, and once every 7 days until the end of gestation at intravenous doses up to 50.6 mg/kg/wk (2.5 times the MRHD on a mg/kg basis). There were no GOHIBIC-related adverse effects on maternal health, pregnancy outcome, embryo-fetal development, or neonatal growth and development up to 6 months of age (PND183). GOHIBIC crossed the placenta in cynomolgus monkeys and GOHIBIC plasma concentrations were similar in infants relative to maternal animals on PND28 and were 8-12 times higher in infants relative to maternal animals on PND91. GOHIBIC was not detected in infant plasma on PND183.

8.2 Lactation

Risk Summary

There are no available data on the presence of GOHIBIC in either human or animal milk, the effects on the breastfed infant, or the effects on milk production.

Maternal IgG is known to be present in human milk. The effects of local gastrointestinal exposure and limited systemic exposure in the breastfed infant to GOHIBIC are unknown.

The lack of clinical data during lactation precludes clear determination of the risk of GOHIBIC to an infant during lactation. Therefore, the developmental and health benefits of breastfeeding should be considered along with the mother's clinical need for GOHIBIC and any potential adverse effects on the breastfed child from GOHIBIC or from the underlying maternal condition.

8.3 Pediatric Use

GOHIBIC is not authorized or approved for the emergency use in pediatric patients for the treatment of coronavirus disease 2019 (COVID-19) in hospitalized patients when initiated within 48 hours of receiving invasive mechanical ventilation (IMV), or extracorporeal membrane oxygenation (ECMO).

8.4 Geriatric Use

Of the total number of GOHIBIC-treated patients in clinical studies for COVID-19 receiving invasive mechanical ventilation (IMV), or extracorporeal membrane oxygenation (ECMO), 53 (30%) were >65 years. No overall differences in effectiveness or safety of GOHIBIC have been observed between patients 65 years of age and older and younger adult patients.

11 DESCRIPTION

Vilobelimab is a chimeric human/mouse immunoglobulin G4 (IgG4) antibody consisting of mouse anti-human complement factor 5a (C5a) monoclonal binding sites (variable regions of heavy and light chain regions), and human gamma 4 heavy chain and kappa light chain constant regions. GOHIBIC is composed of 1,328 amino acids, and the glycosylated intact protein has an approximate molecular weight of 149 kDa produced in Chinese Hamster Ovary (CHO) cell line genetically engineered using ribonucleic acid transfer through a retro-vector system.

GOHIBIC (vilobelimab) injection is a clear to slightly opalescent, colorless solution for intravenous infusion after further dilution. GOHIBIC is provided in single-dose vials at a concentration of 200 mg/20 mL (10 mg/mL). Each mL also contains dibasic sodium phosphate (0.97 mg), monobasic sodium phosphate (0.4 mg), polysorbate 80 (0.5 mg), sodium chloride (8.8 mg), and Water for Injection. The pH is 6.6 – 7.3.

12 CLINICAL PHARMACOLOGY

12.1 Mechanism of Action

GOHIBIC is a chimeric monoclonal IgG4-kappa antibody that binds to C5a with a dissociation constant of 9.6pM and blocks its interaction with the C5a receptor. C5a is part of the complement system and is activated as part of the innate immune response initiating an inflammatory cascade that includes increased vascular permeability, coagulation, proinflammatory cytokine release, and recruitment and activation of neutrophils and other myeloid cells.

12.2 Pharmacodynamics

The reduction of C5a plasma concentration was evaluated in PANAMO. The median plasma concentrations of C5a at baseline in patients with severe COVID-19 pneumonia requiring IMV or ECMO were elevated and the values were comparable between the GOHIBIC group (118.29 ng/mL) and the placebo group (104.62 ng/mL). In the GOHIBIC group, the median concentrations of C5a decreased to 14.53 ng/mL by Day 8 and remained at approximately this level up to Day 30 after the initiation of treatment. In the placebo group, the median concentrations of C5a remained approximately at the baseline level during the study up to Day 30 after the initiation of the treatment. However, the direct clinical relevance of C5a plasma concentration reduction is unclear.

12.3 Pharmacokinetics

In healthy subjects, following a single intravenous infusion of GOHIBIC ranging from 2 mg/kg to 4 mg/kg, GOHIBIC Cmaxshowed dose proportionality while the AUC showed greater than dose proportionality. The elimination half-life of GOHIBIC following a 4 mg/kg single intravenous dose in healthy subjects was 95 hours.

Pre-dose plasma samples were collected in patients with severe COVID-19 pneumonia requiring IMV or ECMO. Following intravenous infusion of GOHIBIC 800 mg on Days 1, 2, and 4, the pre-dose geometric mean (geometric CV%) plasma concentration of GOHIBIC on Day 8 was 137.9 µg/mL (51%).

Drug Interaction Studies

No drug interaction studies have been conducted with GOHIBIC.

12.6 Immunogenicity

The observed incidence of anti-drug antibodies is highly dependent on the sensitivity and specificity of the assay. Differences in assay methods preclude meaningful comparisons of the incidence of anti-drug antibodies in the study described below with incidence of anti-drug antibodies in other studies, including those of GOHIBIC or of other vilobelimab products.

In the Phase 3 clinical study, 2 patients developed treatment-induced anti-drug antibodies; one patient in the GOHIBIC group and one patient in the placebo group. The clinical relevance of the presence of anti-drug antibodies is unclear.

13 NONCLINICAL TOXICOLOGY

13.1 Carcinogenesis, Mutagenesis, Impairment of Fertility

Animal studies have not been conducted to evaluate the carcinogenic potential of GOHIBIC. The malignancy risk in humans from an antibody that binds C5a, such as GOHIBIC, is currently unknown.

Male and female fertility parameters were evaluated as part of the 13-week and 26-week repeat-dose toxicity studies, respectively. There were no treatment-related changes to sperm morphology, count, or motility in male monkeys administered GOHIBIC for 13-weeks at intravenous doses up to 50.6 mg/kg/week (approximately 2.5 times the MRHD on a mg/kg basis). Following 26-weeks intravenous administration of GOHIBIC, there were no effects on female fertility including menstrual cyclicity identified at doses up to 50 mg/kg/week (approximately 2.5 time the MRHD on a mg/kg basis).

14 CLINICAL STUDIES

Clinical data supporting this EUA are based on PANAMO (NCT04333420), a Phase 3, double-blind, randomized, placebo-controlled multicenter trial evaluating GOHIBIC for the treatment of COVID-19 in adult (≥ 18 years) patients requiring IMV or ECMO. The multinational trial was conducted in Europe, Latin America, Russia, and South Africa. Efficacy analyses were based on 368 patients, 177 in the GOHIBIC group and 191 in the placebo group. The mean age of participation was 56 years [range: 22 to 81 years] and 68.5% were male. Common co-existing medical conditions included hypertension (46.2%), obesity (40.8%) and diabetes (29.6%) in the overall study population. All patients were mechanically ventilated and three patients in each arm were on ECMO. Additional demographics and baseline characteristics of patients in PANAMO are provided in Table 2.

Table 2. Demographics and Baseline Characteristics of Patients in PANAMO
 | GOHIBIC + SoC [A total of 369 patients were randomized in the trial (178 to GOHIBIC and 191 to placebo), but one patient in the GOHIBIC group was randomized in error and not included in the efficacy analyses.] (N=177) | Placebo + SoC (N=191)
Age Group, n (%)
18 – 39 years | 22 (12.4%) | 30 (15.7%)
40 – 65 years | 102 (57.6%) | 103 (53.9%)
> 65 years | 53 (29.9%) | 58 (30.4%)
WHO 8-point ordinal scale score [World Health Organization 8-point ordinal scale]
6 – Intubation and mechanical ventilation | 72 (40.7%) | 59 (30.9%)
7 – Ventilation + additional organ support (vasopressors, renal replacement therapy, ECMO) | 105 (59.3%) | 132 (69.1%)
Prior and concomitant medications
Dexamethasone or systemic corticosteroid | 176 (99.4%) | 188 (98.4%)
Baricitinib | 6 (3.4%) | 6 (3.1%)
Tocilizumab | 30 (16.9%) | 31 (16.2%)
Remdesivir | 10 (5.6%) | 11 (5.8%)

The primary endpoint in the study was time to death through Day 28. The Kaplan-Meier estimated 28-Day mortality rate in the GOHIBIC group was 31.7% and the estimated rate in the placebo group was 41.6%, resulting in a hazard ratio of 0.67 (95% CI [0.48, 0.96], p<0.05, Table 3). Results were similar at Day 60 (Table 3). Mortality through day 28 and 60 in PANAMO are provided in Table 3. The percentage of patients alive and either discharged from the hospital or no longer requiring supplemental oxygen at Day 28 were comparable in the GOHIBIC (35.0%) and placebo (36.1%) groups.

Table 3. Mortality through Day 28 and Day 60 in PANAMO
 | GOHIBIC + SoC (N=177) | Placebo + SoC (N= 191)
Day 28 Mortality
Number of Deaths | 54 | 77
Percentage with Death [Results from Kaplan-Meier estimates. Percentages will not be proportional to the number of deaths divided by the total number of patients due to missing values (8 patients missing mortality status in GOHIBIC + SoC and 9 in placebo + SOC).] | 31.7% | 41.6%
Hazard Ratio [Results from Cox proportional hazards regression with treatment and age as covariates. P-values < 0.05.] (95% CI) | 0.67 (0.48, 0.96)
Risk Difference [Results based on a logistic regression model with treatment and age as covariates, and missing values handled by multiple imputation.] (95% CI) | -11.2% (-21.0%, -1.4%)
Day 60 Mortality
Number of Deaths | 62 | 87
Percentage with Death | 36.5% | 47.2%
Hazard Ratio (95% CI) | 0.67 (0.48, 0.93)
Risk Difference (95% CI) | -12.2% (-22.0%, -2.4%)
Abbreviations: CI = confidence interval

16 HOW SUPPLIED/STORAGE AND HANDLING

How supplied

GOHIBIC (vilobelimab) 200 mg/20 mL (10 mg/mL) injection is a clear to slightly opalescent, colorless solution in a single-dose vial (NDC 83000-110-04).

Storage and Handling

Store unopened vials refrigerated at 2°C to 8°C (36°F to 46°F) in the original carton to protect from light. Do not freeze. Do not shake.

17 PATIENT COUNSELING INFORMATION

As a healthcare practitioner, you must communicate to the patient and/or caregiver information consistent with the "FACT SHEET FOR PATIENTS AND CAREGIVERS" and provide them with a copy of this Fact Sheet prior to administration of GOHIBIC. However, if providing this information will delay administration of GOHIBIC to a degree that would endanger the life of a patient, then information must be provided to the caregiver as soon as feasible after GOHIBIC administration.

18 MANUFACTURER INFORMATION

Manufactured by InflaRx GmbH, Winzerlaer Street 2, 07745 Jena, Germany.

©2023 InflaRx GmbH. All rights reserved.

Fact Sheet for Patients and Caregivers

Emergency Use Authorization (EUA) of GOHIBIC for Coronavirus Disease 2019 (COVID-19)

You are being given this Fact Sheet because your healthcare provider believes it is necessary to provide you with GOHIBIC (vilobelimab) for the treatment of coronavirus disease 2019 (COVID-19). Taking GOHIBIC may benefit adults in the hospital with COVID-19 who require a machine that helps with breathing (invasive mechanical ventilation) or a machine that adds oxygen to the blood outside the body (extracorporeal membrane oxygenation or ECMO). This Fact Sheet contains information to help you understand the potential risks and potential benefits of receiving GOHIBIC.

The U.S. Food and Drug Administration (FDA) has issued an Emergency Use Authorization (EUA) to make GOHIBIC available for use as a treatment for certain adults with COVID-19 (for more details about EUA please see " What is an Emergency Use Authorization?" at the end of this document). GOHIBIC is not FDA-approved for this use. Read this Fact Sheet for information about GOHIBIC. Talk to your healthcare provider about your options or if you have any questions. It is your choice for you to take GOHIBIC or stop it at any time.

What is COVID-19?

COVID-19 is caused by a virus called a coronavirus. You can get COVID-19 through contact with another person who has the virus.

COVID-19 illnesses have ranged from very mild (including some with no reported symptoms) to severe, including illness resulting in death. While information so far suggests that most COVID-19 illness is mild, serious illness can happen and may cause some of your other medical conditions to become worse. People of all ages with severe, long-lasting (chronic) medical conditions like heart disease, lung disease, and diabetes, for example, seem to be at higher risk of being hospitalized for COVID-19.

What are the symptoms of COVID-19?

The symptoms of COVID-19 may include fever, cough, and shortness of breath, which can appear 2 to 14 days after exposure. Serious illness, including breathing problems, can occur and may cause your other medical conditions to become worse.

What is GOHIBIC?

GOHIBIC is an investigational medicine used for the treatment of COVID-19 in hospitalized adults when initiated within 48 hours of receiving invasive mechanical ventilation or extracorporeal membrane oxygenation (ECMO). GOHIBIC is investigational because it is still being studied. GOHIBIC is not FDA-approved to treat COVID-19.

There is limited information known about the safety or effectiveness of using GOHIBIC to treat people in the hospital with COVID-19. Available results from clinical trials in adults indicate that treatment with GOHIBIC may decrease the risk of dying in hospitalized adults with COVID-19 when initiated within 48 hours of receiving invasive mechanical ventilation or ECMO. The safety and effectiveness of GOHIBIC have not been studied in children hospitalized with COVID-19.

The FDA has authorized the emergency use of GOHIBIC for the treatment of COVID-19 in hospitalized adults when initiated within 48 hours of receiving invasive mechanical ventilation or ECMO under an EUA. For more information on EUA, see the " What is an Emergency Use Authorization (EUA)?" section at the end of this Fact Sheet.

What should I tell my healthcare provider before I receive GOHIBIC?

Tell your healthcare provider about all of your medical conditions including if you:

- Have allergies.
- Have an infection other than COVID-19.
- Are pregnant or plan to become pregnant.
- Are breast-feeding or plan to breastfeed.
- Have any serious illnesses.

Tell your healthcare provider about all the medicines you take, including prescription and, over-the-counter medicines, vitamins, and herbal supplements.

How will I receive GOHIBIC?

GOHIBIC is given to you through a vein (intravenous or IV) as an infusion. GOHIBIC will be given up to six doses. The first dose will be given within 48 hours of a tube being inserted (intubation) and a machine to help you breathe (ventilator), this is Day 1. The following administration of GOHIBIC will be given on Days 2, 4, 8, 15, and 22 as long as you are hospitalized [even discharged from the Intensive Care Unit (ICU)].

What are the important possible side effects of GOHIBIC?

GOHIBIC may cause serious side effects, including:

- Serious infections: GOHIBICis a medicine that affects your immune system. GOHIBICcan lower the ability of your immune system to fight infections other than COVID-19.
- Allergic Reactions:Serious allergic reactions can happen during or after treatment with GOHIBIC. These reactions may be severe or life-threatening.
  Signs and symptoms of a serious allergic reaction with GOHIBIC may include:
  - trouble breathing
  - rash
  - swelling of your face, eyes, lips mouth, tongue and throat.

The most common side effects of GOHIBIC may include:Lung infection, sepsis, sudden confusion, sudden lung artery blockage, high blood pressure, collapsed lung, venous blood clotting (usually in the leg), herpes infection, certain infections caused by enterococci, urinary tract infection, low blood oxygenation, low platelets, the presence of air in the space in the chest between the two lungs, infection of the respiratory tract, heart arrythmia, constipation, and rash.

What other treatment choices are there?

Olumiant (baricitinib), Actemra (tocilizumab), and Veklury (remdesivir) are FDA-approved medicines for the treatment of COVID-19 in hospitalized patients who require invasive mechanical ventilation or ECMO. Talk with your healthcare provider to see if those therapies are appropriate for you. Like GOHIBIC, FDA may allow for the emergency use of other medicines to treat people in the hospital with COVID-19. Go to https://www.fda.gov/emergency-preparedness-and-response/mcm-legal-regulatory-and-policy-framework/emergency-use-authorization for information on emergency use of other medicines that are not approved by FDA to treat people in the hospital with COVID-19. Please consult with your healthcare provider on which medicine or combination of medicines might be right for you. Your healthcare provider may talk with you about clinical trials you may be eligible for.

It is your choice to be treated or not to be treated with GOHIBIC. Should you decide not to receive it, it will not change your standard medical care.

What if I am pregnant or breastfeeding?

There is no experience giving GOHIBIC to pregnant women or breastfeeding mothers. GOHIBIC may harm your unborn baby. It is unknown if GOHIBIC passes into your breast milk. If you are pregnant or breastfeeding, discuss your options and specific situation with your healthcare provider.

How do I report side effects or adverse events with GOHIBIC?

Contact your healthcare provider if you have any side effects that bother you or do not go away. Report side effects to FDA MedWatch at www.fda.gov/medwatch or call 1-800-FDA-1088. You may also report side effects to InflaRx GmbH by calling 1-888-254-0602.

How can I learn more about COVID-19?

- Ask your healthcare provider
- Visit https://www.cdc.gov/COVID19
- Contact your local or state public health department

What is an Emergency Use Authorization (EUA)?

The United States FDA has made GOHIBIC available under an emergency access mechanism called an EUA. The EUA is supported by a Secretary of Health and Human Service (HHS) declaration that circumstances exist to justify the emergency use of drugs and biological products during the COVID-19 pandemic.

GOHIBIC, as a treatment for COVID-19 has not undergone the same type of review as an FDA-approved product for this indication. The FDA may issue an EUA when certain criteria are met, which includes that there are no adequate, approved, and available alternatives. In addition, the FDA decision is based on the totality of scientific evidence available showing that it is reasonable to believe that the product meets certain criteria for safety, performance, and labeling and may be effective in treatment of patients during the COVID-19 pandemic.

All of these criteria must be met to allow for the product to be used in the treatment of patients during the COVID-19 pandemic.

The EUA for GOHIBIC as a treatment for certain people with COVID-19 is in effect for the duration of the COVID-19 declaration justifying emergency use of this product, unless terminated or revoked (after which the products may no longer be used under the EUA).

This Fact Sheet may be updated as new data become available. The most recent version of this Fact Sheet is available at www.gohibic.com .

Manufactured by:
InflaRx GmbH
Winzerlaer Street 2
07745 Jena
Germany

© 2023, InflaRx. All rights reserved.
Authorized: 04/2023

PRINCIPAL DISPLAY PANEL - 200 mg/20 mL Vial Carton

NDC 83000-110-04
Rx-only

GOHIBIC
(vilobelimab)
injection

200 mg/20 mL
(10 mg/mL)

For intravenous infusion after dilution

For use under Emergency Use Authorization

4 x 20 mL single-dose vials-Discard unused portion